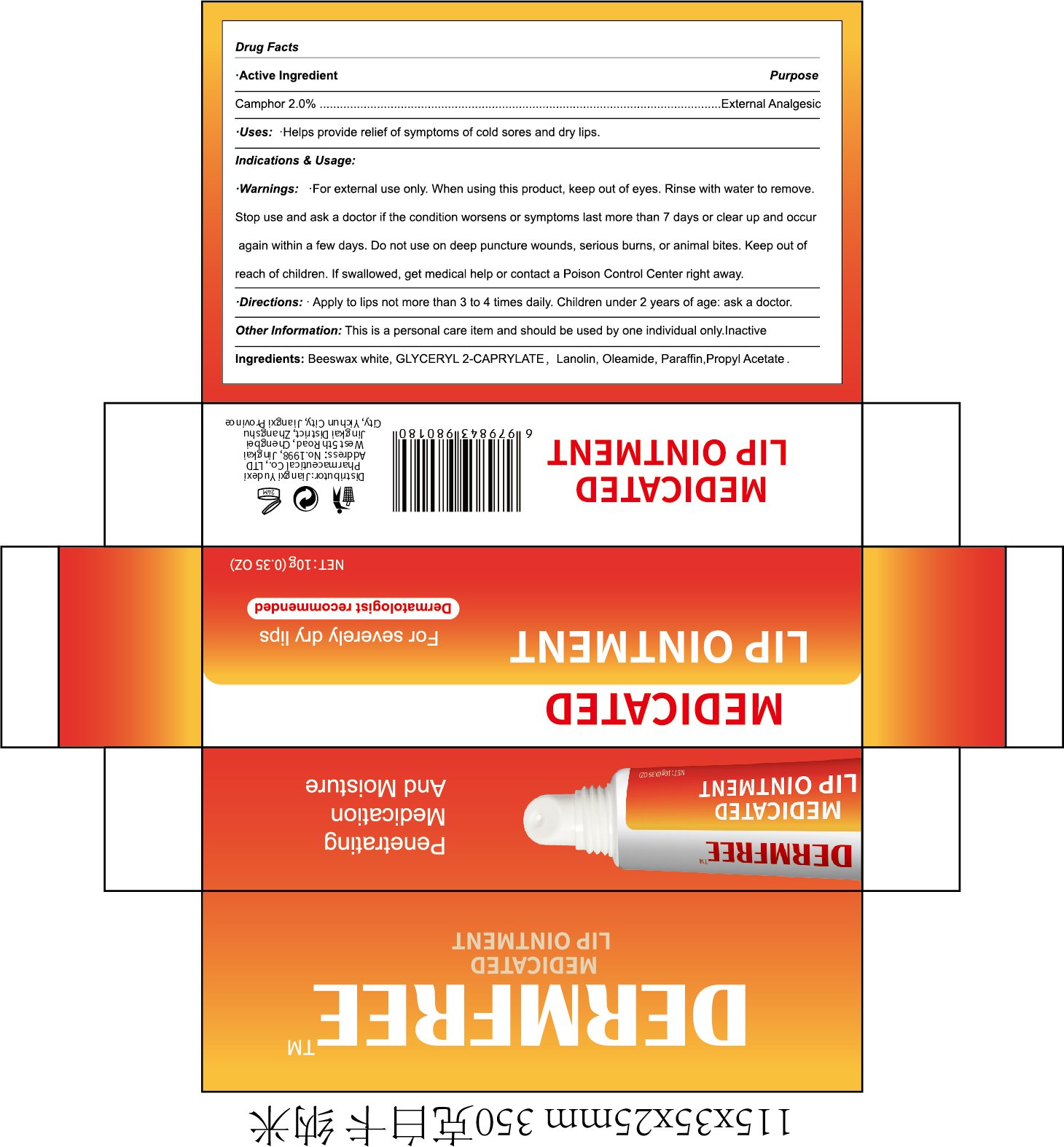 DRUG LABEL: DERMFREE MEDICATED LIP
NDC: 85248-113 | Form: OINTMENT
Manufacturer: Jiangxi Yudexi Pharmaceutical Co., LTD
Category: otc | Type: HUMAN OTC DRUG LABEL
Date: 20260208

ACTIVE INGREDIENTS: CAMPHOR (SYNTHETIC) 2 g/100 g
INACTIVE INGREDIENTS: OLEAMIDE; PARAFFIN; WHITE WAX; GLYCERYL 2-CAPRYLATE; LANOLIN; PROPYL ACETATE

85248-113

Active Ingredient

Camphor 2.%.

Purpose

External Analgesic

Use

Helps provide relief of symptoms of cold sores and dry lips.

Warnings

·For external use only, When using this product, keep out of eyes. Rinse with water to remove

Do not use on deep puncture wounds,serious burns, or animal bites. Keep out of reach of children. If swallowed, get medical help or contact a Poison Control Center right away.

When Using

·For external use only, When using this product, keep out of eyes. Rinse with water to remove

Stop Use

Stop use and ask a doctor if the condition worsens or symptoms last more than 7 days or clear up and occur again within a few days

Ask Doctor

if the condition worsens or symptoms last more than 7 days or clear up and occur again within a few days.
Children under 2 years of age

Keep Oot Of Reach Of Children

If swallowed, get medical help or contact a Poison Control Center right away.

Directions

Apply to lips not more than 3 to 4 times daily. Children under 2 years of age: ask a doctor.

Other information

This is a personal care item and should be used by one individual only.

Inactive ingredients

Beeswax white, GLYCERYL 2-CAPRYLATE, Lanolin,Oleamide, Paraffin,Propyl Acetate.